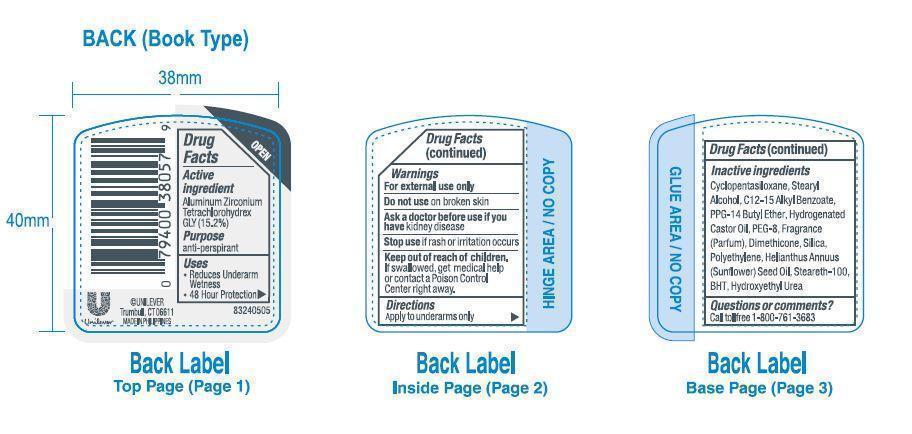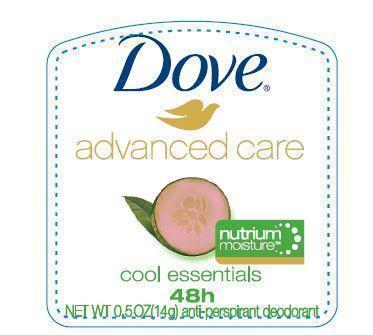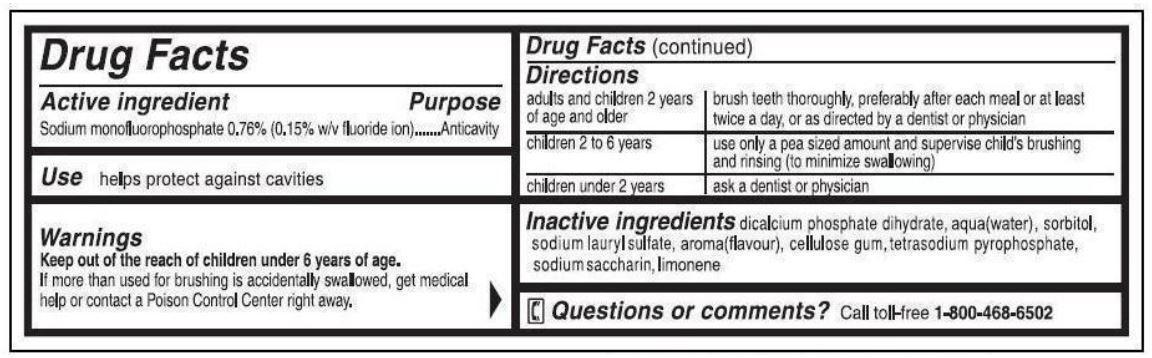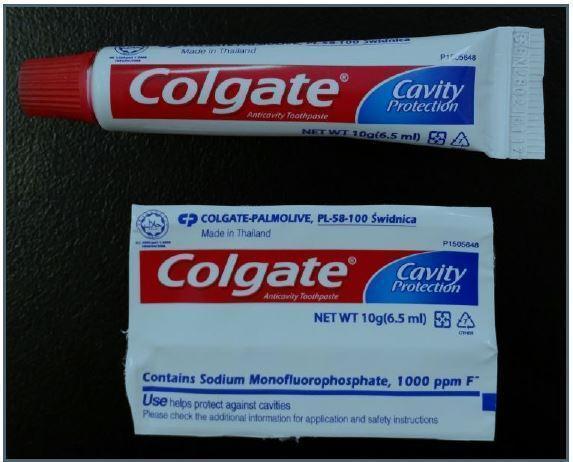 DRUG LABEL: RON 2
NDC: 69491-030 | Form: KIT | Route: DENTAL
Manufacturer: Buzz Export Services Pty., Ltd.
Category: otc | Type: HUMAN OTC DRUG LABEL
Date: 20211227

ACTIVE INGREDIENTS: SODIUM MONOFLUOROPHOSPHATE 7.6 mg/1 g; ALUMINUM ZIRCONIUM TETRACHLOROHYDREX GLY 15.2 g/100 g
INACTIVE INGREDIENTS: CALCIUM PHOSPHATE, DIBASIC, DIHYDRATE; WATER; SORBITOL; SODIUM LAURYL SULFATE; CARBOXYMETHYLCELLULOSE SODIUM, UNSPECIFIED FORM; SODIUM PYROPHOSPHATE; SACCHARIN SODIUM; CYCLOMETHICONE 5; STEARYL ALCOHOL; ALKYL (C12-15) BENZOATE; PPG-14 BUTYL ETHER; HYDROGENATED CASTOR OIL; POLYETHYLENE GLYCOL 400; DIMETHICONE; SILICON DIOXIDE; HIGH DENSITY POLYETHYLENE; SUNFLOWER OIL; STEARETH-100; BUTYLATED HYDROXYTOLUENE; HYDROXYETHYL UREA

RON Kit 2

Active ingredient

Sodium monofluorophosphate 0.76% (0.15% w/v fluoride ion)

Purpose

Anticavity

Warnings

Keep out of the reach of children under 6 years of age.

If more than used for brushing is accidentally swallowed, get medical help or contact a Poison Control Center right away.

Directions

adults and children 2 years of age and older | brush teeth thoroughly preferably after each meal or at least twice a day, or as directed by a dentist or physician
children 2 to 6 years | use only a pea sized amount and supervise child's brushing and rinsing (to minimize swallowing)
children under 2 years | ask a dentist or physician

Inactive ingredients

dicalcium phosphate dihydrate, aqua(water), sorbitol, sodium lauryl sulfate, aroma(flavor), cellulose gum, tetrasodium pyrophosphate, sodium saccharin, limonene

Questions or comments?

Call toll-free 1-800-468-6502

Active ingredient

Aluminum Zirconium Tetrachlorohydrex GLY (15.2%)

Purpose

anti-perspirant

Uses

- Reduces Underarm Wetness
- 48 Hour Protection

Warnings

For external use only

Do not use on broken skin

Ask a doctor before use if you have kidney disease.

Stop use if rash or irritation occurs.

Keep out of reach of children.

If swallowed, get medical help or contact a Poison Control Center right away.

Directions

Apply to underarms only

Inactive ingredients

Cyclopentasiloxane, Stearyl Alcohol, C12-15 Alkyl Benzoate, PPG-14 Butyl Ether, Hydrogenated Castor Oil, PEG-8, Fragrance (Parfum), Dimethicone, Silica, Polyethylene, Helianthus Annuus (Sunflower) Seed Oil, Steareth-100, BHT, Hydroxyethyl Urea

Questions or comments?

Call toll free 1-800-761-3683